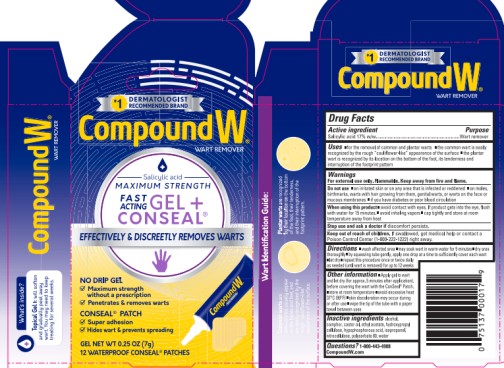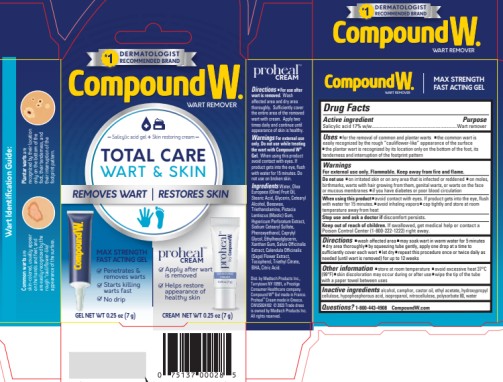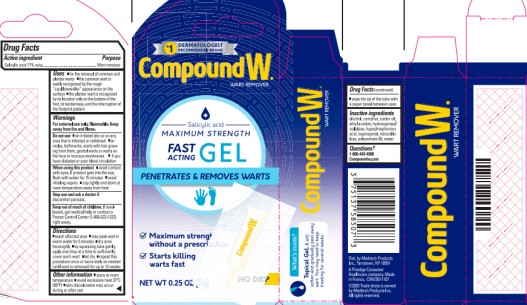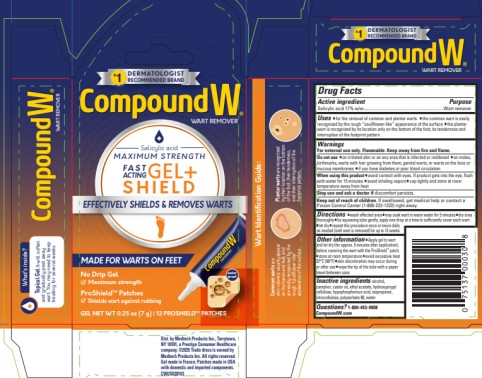 DRUG LABEL: Compound W
NDC: 63029-595 | Form: GEL
Manufacturer: Medtech Products Inc.
Category: otc | Type: HUMAN OTC DRUG LABEL
Date: 20251023

ACTIVE INGREDIENTS: SALICYLIC ACID 170 mg/1 g
INACTIVE INGREDIENTS: ALCOHOL; CAMPHOR (NATURAL); CASTOR OIL; ETHYL ACETATE; HYDROXYPROPYL CELLULOSE (1600000 WAMW); HYPOPHOSPHOROUS ACID; ISOPROPYL ALCOHOL; PYROXYLIN; POLYSORBATE 80; WATER

Compound W Gel

Compound W®
Salicylic Acid Wart Remover

MAXIMUM STRENGTH
FAST ACTING GEL

NET WT 0.25 OZ (7 g)

Drug Facts

Active ingredient

Salicylic acid 17% w/w

Purpose

Wart remover

Use

- for the removal of common and plantar warts
- the common wart is easily recognized by the rough “cauliflower-like” appearance on the surface
- the plantar wart is recognized by its location only on the bottom of the foot, its tenderness, and the interruption of the footprint pattern

Warnings

For external use only.

Flammable. Keep away from fire and flame.

Do not use

- on irritated skin or on any area that is infected or reddened
- on moles, birthmarks, warts with hair growing from them, genital warts or warts on the face or mucous membranes
- if you have diabetes or poor blood circulation

When using this product

- avoid contact with eyes. If product gets into the eye, flush with water for 15 minutes.
- avoid inhaling vapors
- cap tightly and store at room temperature away from heat

Stop use and ask a doctor if

discomfort persists.

Keep out of reach of children.

If swallowed, get medical help or contact a Poison Control Center (1-800-222-1222) right away.

Directions

- wash affected area
- may soak wart in warm water for 5 minutes
- dry area thoroughly
- by squeezing tube gently, apply one drop at a time to sufficiently cover each wart
- let dry
- repeat this procedure once or twice daily as needed (until wart is removed) for up to 12 weeks

Other Information

- store at room temperature
- avoid excessive heat 37°C (99°F)
- skin discoloration may occur during or after use
- wipe the tip of the tube with a paper towel between uses

Inactive ingredients

alcohol, camphor, castor oil, ethyl acetate, hydroxypropyl cellulose, hypophosphorous acid, isopropanol, nitrocellulose, polysorbate 80, water

Questions?

1-800-443-4908 CompoundW.com

PRINCIPAL DISPLAY PANEL

Compound W
WART REMOVER SYSTEM
MAXIMUM STRENGTH
FAST ACTING GEL + CONSEAL
Salicylic acid
NET WT 0.25 OZ (7g)

PRINCIPAL DISPLAY PANEL

Compound W
Total Care Wart & Skin
Salicylic acid – Wart Remover
GEL NET WT 0.25 OZ (7g)

PRINCIPAL DISPLAY PANEL

Compound W
Wart Remover
Salicylic acid
MAXIMUM STRENGTH
GEL
NET WT 0.25 OZ (7g)

PRINCIPAL DISPLAY PANEL

Compound W
Wart Remover

Gel + Shield
Gel Net Wt 0.25 oz (7g) I 12 proshield patches